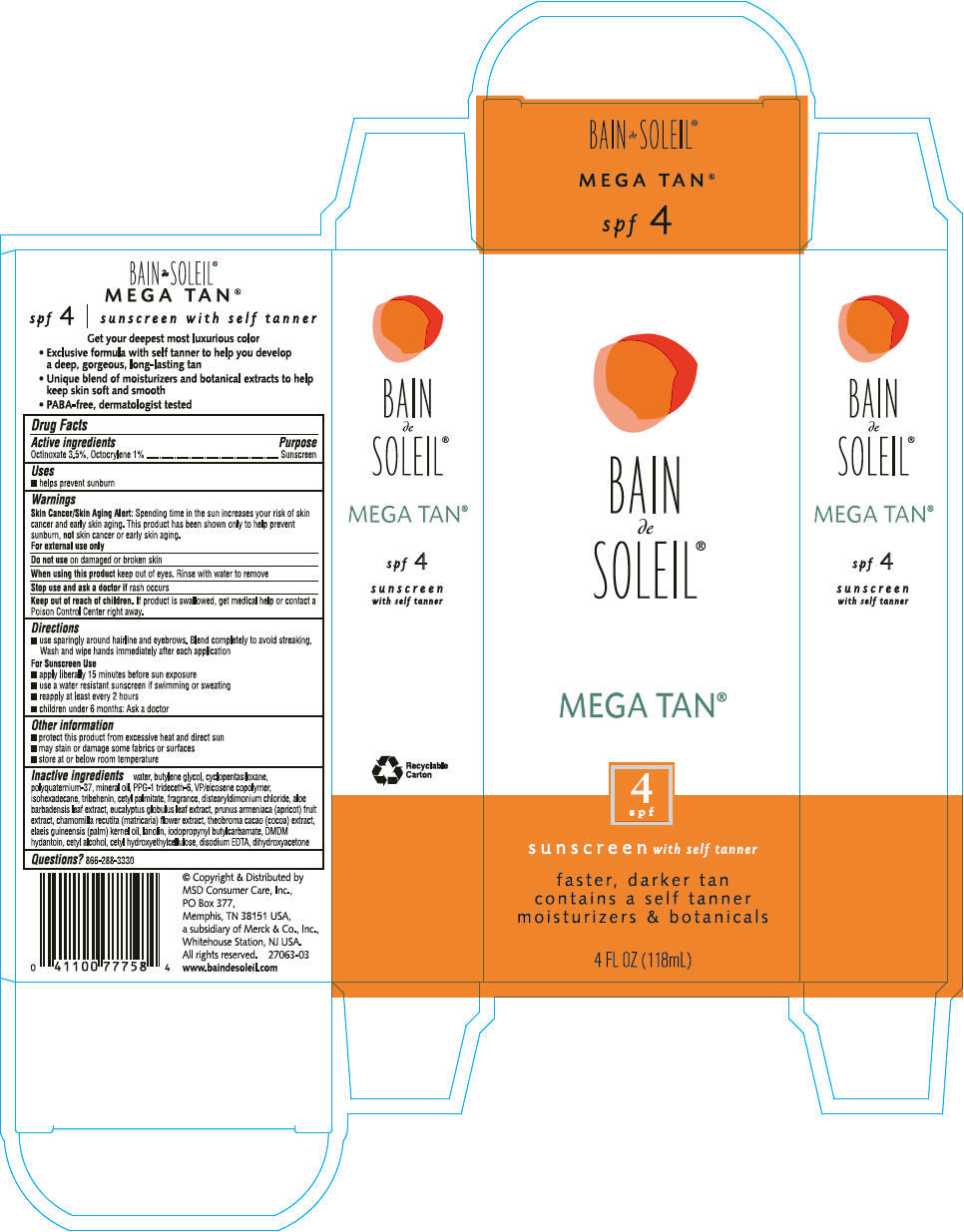 DRUG LABEL: Bain de Soleil
NDC: 11523-7094 | Form: LOTION
Manufacturer: Bayer HealthCare LLC.
Category: otc | Type: HUMAN OTC DRUG LABEL
Date: 20230908

ACTIVE INGREDIENTS: OCTINOXATE 35 mg/1 mL; OCTOCRYLENE 10 mg/1 mL
INACTIVE INGREDIENTS: WATER; BUTYLENE GLYCOL; CYCLOMETHICONE 5; MINERAL OIL; PPG-1 TRIDECETH-6; ISOHEXADECANE; TRIBEHENIN; CETYL PALMITATE; DISTEARYLDIMONIUM CHLORIDE; ALOE VERA LEAF; EUCALYPTUS GLOBULUS LEAF; APRICOT; CHAMOMILE; COCOA; PALM KERNEL OIL; LANOLIN; IODOPROPYNYL BUTYLCARBAMATE; DMDM HYDANTOIN; CETYL ALCOHOL; EDETATE DISODIUM; DIHYDROXYACETONE

Bain de Soleil®
Mega Tan® SPF 4

Drug Facts

Active ingredient

Octinoxate 3.5%, Octocrylene 1%

Purpose

Sunscreen

Use

- helps prevent sunburn

Warnings

Skin Cancer/Skin Aging Alert

Spending time in the sun increases your risk of skin cancer and early skin aging. This product has been shown only to help prevent sunburn, not skin cancer or early skin aging.

For external use only

Do not use on damaged or broken skin

When using this product keep out of eyes. Rinse with water to remove

Stop use and ask a doctor if rash occurs

Keep out of reach of children. If product is swallowed, get medical help or contact a Poison Control Center right away.

Directions

- use sparingly around hairline and eyebrows. Blend completely to avoid streaking. Wash and wipe hands immediately after each application

For Sunscreen Use

- apply liberally 15 minutes before sun exposure
- use a water resistant sunscreen if swimming or sweating
- reapply at least every 2 hours
- children under 6 months: Ask a doctor

Other information

- protect this product from excessive heat and direct sun
- may stain or damage some fabrics or surfaces

- store at or below room temperature

Inactive ingredients

water, butylene glycol, cyclopentasiloxane, polyquaternium-37, mineral oil, PPG-1 trideceth-6, VP/eicosene copolymer, isohexadecane, tribehenin, cetyl palmitate, fragrance, distearyldimonium chloride, aloe barbadensis leaf extract, eucalyptus globulus leaf extract, prunus armeniaca (apricot) fruit extract, chamomilla recutita (matricaria) flower extract, theobroma cacao (cocoa) extract, elaeis guineensis (palm) kernel oil, lanolin, iodopropynyl butylcarbamate, DMDM hydantoin, cetyl alcohol, cetyl hydroxyethylcellulose, disodium EDTA, dihydroxyacetone

Questions?

866-288-3330

PRINCIPAL DISPLAY PANEL - 118 mL Tube Carton

BAIN
de
SOLEIL®

MEGA TAN®

4
spf

sunscreen with self tanner

faster, darker tan
contains a self tanner
moisturizers & botanicals

4 FL OZ (118mL)